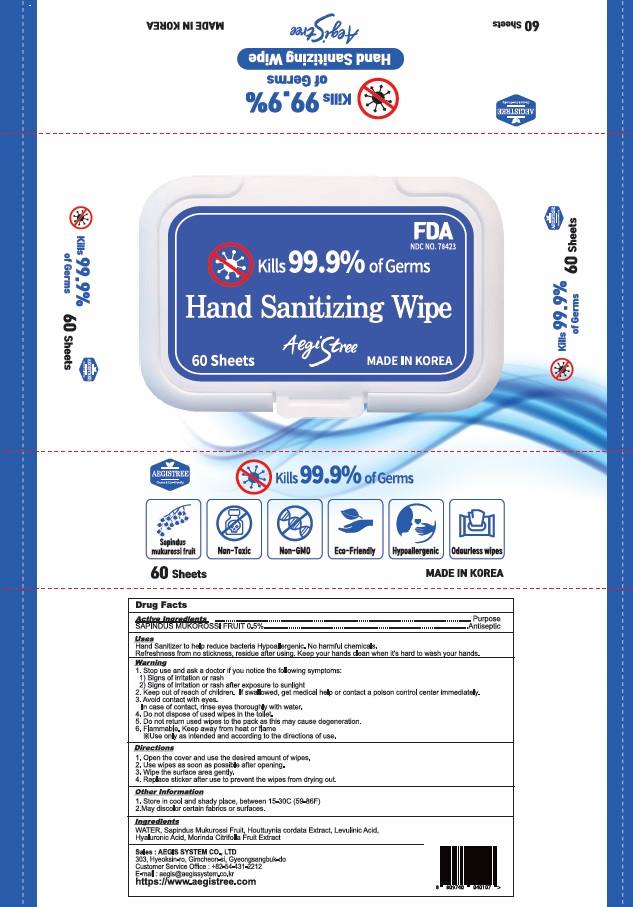 DRUG LABEL: AEGIS TREE hand sanitizing wipe
NDC: 78423-0005 | Form: CLOTH
Manufacturer: AEGIS SYSTEM CO.,LTD
Category: otc | Type: HUMAN OTC DRUG LABEL
Date: 20200703

ACTIVE INGREDIENTS: SAPINDUS MUKOROSSI FRUIT 0.5 1/100 1
INACTIVE INGREDIENTS: Water; MORINDA CITRIFOLIA LEAF; HOUTTUYNIA CORDATA FLOWERING TOP; HYALURONIC ACID; LEVULINIC ACID

ACTIVE INGREDIENT

SAPINDUS MUKOROSSI FRUIT 0.5%

INACTIVE INGREDIENTS

Water, HOUTTUYNIA CORDATA EXTRACT, LEVULINIC ACID, HYALURONIC ACID, MORINDA CITRIFOLIA FRUIT EXTRACT

PURPOSE

Antiseptic

WARNING

1. Stop use and ask a doctor if signs symptoms as follows
(1) signs of irritation and/or rash appears
(2) signs of abnormality as above after exposed to sunlight.
2. Keep out of reach of children. If swallowed, get medical help Or contact a Poison Control Center right away.
3. Avoid contact with eyes.
In case of contact, rinse eyes thoroughly with water.
4. Do not dispose used tissue in the flushing toilet
5. Do not put used tissue into pack again.
There is the risk of degeneration.
6. Flammable. Keep away from heat or flame
※Use only as intended and according to the directions of use.

KEEP OUT OF REACH OF CHILDREN

If swallowed, get medical help or contact a Poison Control Center right away.

Uses

Hand Sanitizer to help reduce bacteria Hypoallergenic. No harmful chemicals. Refreshness from no stickness, residue after using. Keep your hands clean when it's hard to wash your hands.

Directions

1. Open the cover and use the desired amount of wipes.
2. Use wipes as soon as possible after opening.
3. Wipe the surface area gently.
4. Replace sticker after use to prevent the wipe from dying out.

Other information

1. Store in cool and shady place, between 15-30C (59-86F)
2.May discolor certain fabrics or surfaces.